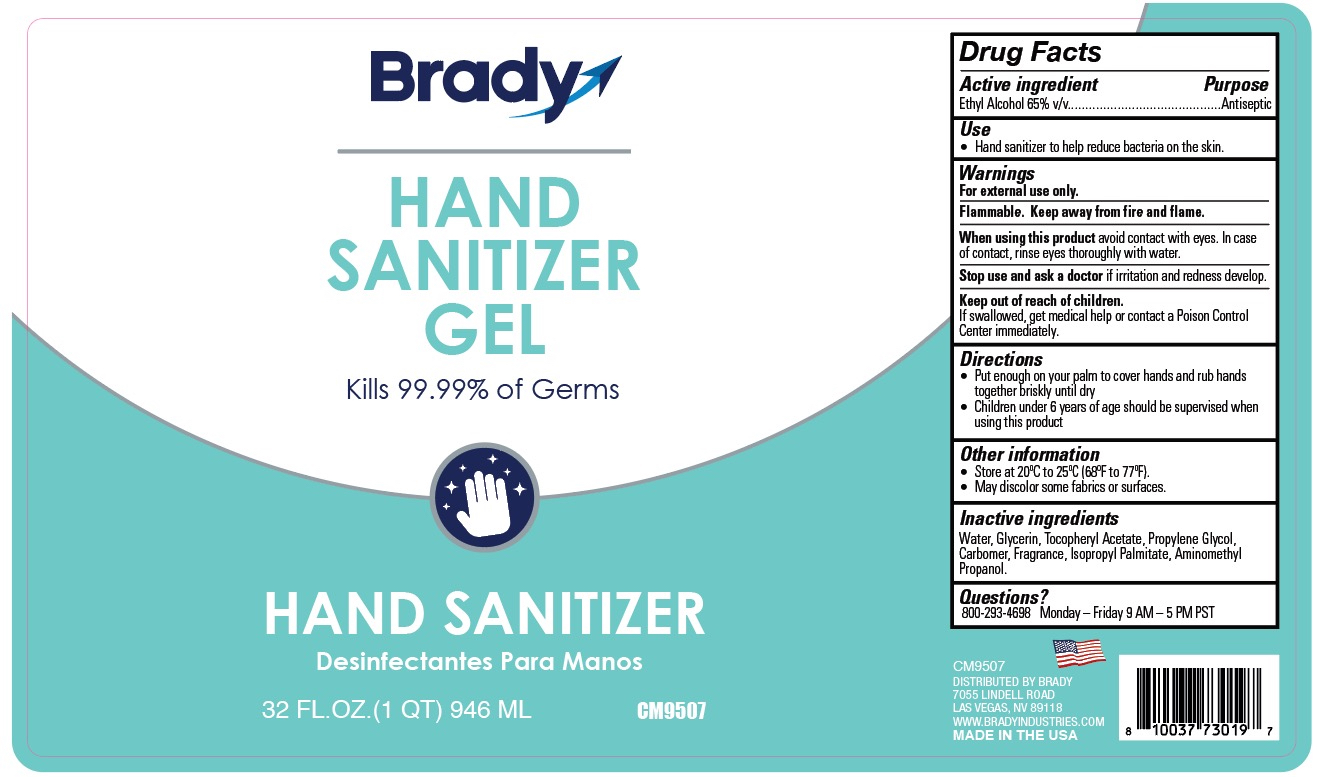 DRUG LABEL: Hand Sanitizer
NDC: 79258-104 | Form: GEL
Manufacturer: Brady Industries, Inc.
Category: otc | Type: HUMAN OTC DRUG LABEL
Date: 20200730

ACTIVE INGREDIENTS: ALCOHOL 65 mL/100 mL
INACTIVE INGREDIENTS: AMINOMETHYLPROPANOL; WATER; GLYCERIN; ALPHA-TOCOPHEROL ACETATE; CARBOMER 934; ISOPROPYL PALMITATE; PROPYLENE GLYCOL

Drug Facts

Active Ingredient(s)

Ethyl Alcohol 65% v/v. Purpose: Antiseptic

Purpose

Antiseptic, Hand Sanitizer

Use

Hand Sanitizer to help reduce bacteria on the skin.

Warnings

For external use only. Flammable. Keep away from fire and flame.

Do not use

- in children less than 2 months of age
- on open skin wounds

When using this product avoid contact with eyes. In case of contact, rinse eyes thoroughly with water.
Stop use and ask a doctor if irritation and redness develops.
Keep out of reach of children. If swallowed, get medical help or contact a Poison Control Center immediately.

Stop use and ask a doctor if irritation or rash occurs. These may be signs of a serious condition.

Keep out of reach of children. If swallowed, get medical help or contact a Poison Control Center right away.

Directions

- Put enought on your palm to cover hand and rub hands together briskly until dry.
- Children under 6 years of age should be supervised when using the product.

Other information

- Store between 20-25C (68-77F)
- May discolor some fabrics or surfaces
- Avoid freezing and excessive heat above 40C (104F)

Inactive ingredients

Water, Glycerin, Propylene Glycol, Carbomer, Fragrance, Isopropyl Palmitate, Aminomethyl Propanol, Tocopheryl Acetate.

Package Label - Principal Display Panel

946ml NDC: 79258-104-32